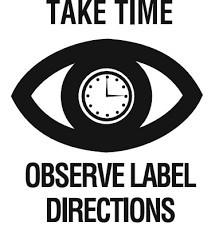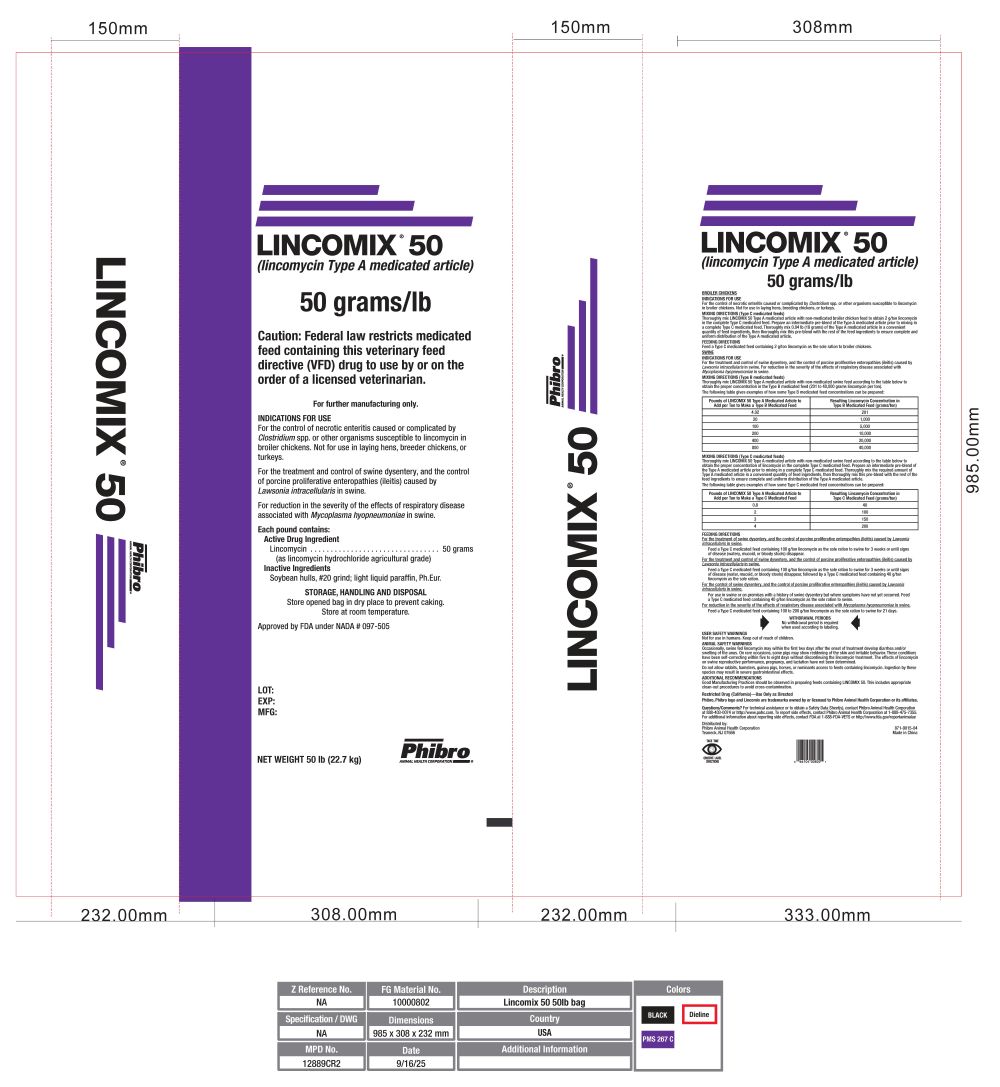 DRUG LABEL: Lincomix 50
NDC: 66104-1494 | Form: GRANULE
Manufacturer: Phibro Animal Health
Category: animal | Type: VFD TYPE A MEDICATED ARTICLE ANIMAL DRUG LABEL
Date: 20260223

ACTIVE INGREDIENTS: LINCOMYCIN HYDROCHLORIDE 50 g/0.453 kg

LINCOMIX® 50(lincomycin)

LINCOMIX® 50

(lincomycin Type A medicated article)

50 grams/lb

Caution: Federal law restricts medicated feed containing this veterinary feed directive (VFD) drug to use by or on the order of a licensed veterinarian.

For further manufacturing only.

INDICATIONS FOR USE

For the control of necrotic enteritis caused or complicated by Clostridium spp. or other organisms susceptible to lincomycin in broiler chickens. Not for use in laying hens, breeder chickens, or turkeys.

For the treatment and control of swine dysentery, and the control of porcine proliferative enteropathies (ileitis) caused by Lawsonia intracellularis in swine.

For reduction in the severity of the effects of respiratory disease associated with Mycoplasma hyopneumoniae in swine.

Each pound contains:

Active Drug Ingredient

Lincomycin.................................50 grams

(as lincomycin hydrochloride agricultural grade)

Inactive Ingredients

Soybean hulls, #20 grind; light liquid paraffin, Ph.Eur.

STORAGE, HANDLING AND DISPOSAL

Store opened bag in dry place to prevent caking. Store at room temperature.

Approved by FDA under NADA # 097-505

LOT:

EXP:

MFG:

NET WEIGHT 50 lb (22.7 kg)

BROILERS

BROILER CHICKENS

INDICATIONS FOR USE

For the control of necrotic enteritis caused or complicated by Clostridium spp. or other organisms susceptible to lincomycin in broiler chickens. Not for use in laying hens, breeding chickens, or turkeys.

MIXING DIRECTIONS (Type C medicated feeds)
Thoroughly mix LINCOMIX 50 Type A medicated article with non-medicated broiler chicken feed to obtain 2 g/ton lincomycin in the complete Type C medicated feed. Prepare an intermediate pre-blend of the Type A medicated article prior to mixing in a complete Type C medicated feed. Thoroughly mix 0.04 lb (18 grams) of the Type A medicated article in a convenient quantity of feed ingredients, then thoroughly mix this pre-blend with the rest of the feed ingredients to ensure complete and uniform distribution of the Type A medicated article.

FEEDING DIRECTIONS
Feed a Type C medicated feed containing 2 g/ton lincomycin as the sole ration to broiler chickens.

SWINE

INDICATIONS FOR USE
For the treatment and control of swine dysentery, and the control of porcine proliferative enteropathies (ileitis) caused by Lawsonia intracellularis in swine. For reduction in the severity of the effects of respiratory disease associated with Mycoplasma hyopneumoniae in swine.

MIXING DIRECTIONS (Type B medicated feeds)
Thoroughly mix LINCOMIX 50 Type A medicated article with non-medicated swine feed according to the table below to obtain the proper concentration in the Type B medicated feed (201 to 40,000 grams lincomycin per ton).

The following table gives examples of how some Type B medicated feed concentrations can be prepared:

Pounds of LINCOMIX 50 Type A Medicated Article to; Add per Ton to Make a Type B Medicated Feed | Resulting Lincomycin Concentration in; Type B Medicated Feed (grams/ton)
4.02 | 201
20 | 1,000
100 | 5,000
200 | 10,000
400 | 20,000
800 | 40,000

MIXING DIRECTIONS (Type C medicated feeds)
Thoroughly mix LINCOMIX 50 Type A medicated article with non-medicated swine feed according to the table below to obtain the proper concentration of lincomycin in the complete Type C medicated feed. Prepare an intermediate pre-blend of the Type A medicated article prior to mixing in a complete Type C medicated feed. Thoroughly mix the required amount of Type A medicated article in a convenient quantity of feed ingredients, then thoroughly mix this pre-blend with the rest of the feed ingredients to ensure complete and uniform distribution of the Type A medicated article.

The following table gives examples of how some Type C medicated feed concentrations can be prepared:

Pounds of LINCOMIX 50 Type A Medicated Article to; Add per Ton to Make a Type C Medicated Feed | Resulting Lincomycin Concentration in; Type C Medicated Feed (grams/ton)
0.8 | 40
2 | 100
3 | 150
4 | 200

FEEDING DIRECTIONS
For the treatment of swine dysentery, and the control of porcine proliferative enteropathies (ileitis) caused by Lawsonia intracellularis in swine.

Feed a Type C medicated feed containing 100 g/ton lincomycin as the sole ration to swine for 3 weeks or until signs of disease (watery, mucoid, or bloody stools) disappear.

For the treatment and control of swine dysentery, and the control of porcine proliferative enteropathies (ileitis) caused by Lawsonia intracellularis in swine.

Feed a Type C medicated feed containing 100 g/ton lincomycin as the sole ration to swine for 3 weeks or until signs of disease (water, mucoid, or bloody stools) disappear, followed by a Type C medicated feed containing 40 g/ton lincomycin as the sole ration.

For the control of swine dysentery, and the control of porcine proliferative enteropathies (ileitis) caused by Lawsonia intracellularis in swine.

For use in swine or on premises with a history of swine dysentery but where symptoms have not yet occurred. Feed a Type C medicated feed containing 40 g/ton lincomycin as the sole ration to swine.

For reduction in the severity of the effects of respiratory disease associated with Mycoplasma hyopneumoniae in swine.

Feed a Type C medicated feed containing 100 to 200 g/ton lincomycin as the sole ration to swine for 21 days.

WITHDRAWAL PERIODS

No withdrawal period is required when used according to labeling.

USER SAFETY WARNING

Not for use in humans. Keep out of reach of children.

ANIMAL SAFETY WARNINGS

Occasionally, swine fed lincomycin may within the first two days after the onset of treatment develop diarrhea and/or swelling of the anus. On rare occasions, some pigs may show reddening of the skin and irritable behavior. These conditions have been self-correcting within five to eight days without discontinuing the lincomycin treatment. The effects of lincomycin on swine reproductive performance, pregnancy, and lactation have not been determined.

Do not allow rabbits, hamsters, guinea pigs, horses, or ruminants access to feeds containing lincomycin. Ingestion by these species may result in severe gastrointestinal effects.

ADDITIONAL RECOMMENDATIONS
Good Manufacturing Practices should be observed in preparing feeds containing LINCOMIX 50. This includes appropriate clean-out procedures to avoid cross-contamination.

Restricted Drug (California)—Use Only as Directed
Phibro, Phibro logo and Lincomix are trademarks owned by or licensed to Phibro Animal Health Corporation or its affiliates.

Questions/Comments? For technical assistance or to obtain a Safety Data Sheet(s), contact Phibro Animal Health Corporation
at 888-403-0074 or http://www.pahc.com. To report side effects, contact Phibro Animal Health Corporation at 1-888-475-7355.
For additional information about reporting side effects, contact FDA at 1-888-FDA-VETS or http://www.fda.gov/reportanimalae

Distributed by:
Phibro Animal Health Corporation 871-9015-04
Teaneck, NJ 07666

871-9015-04

Made in China

Take time statement

PRINCIPAL DISPLAY PANEL

Lincomix 50 Label